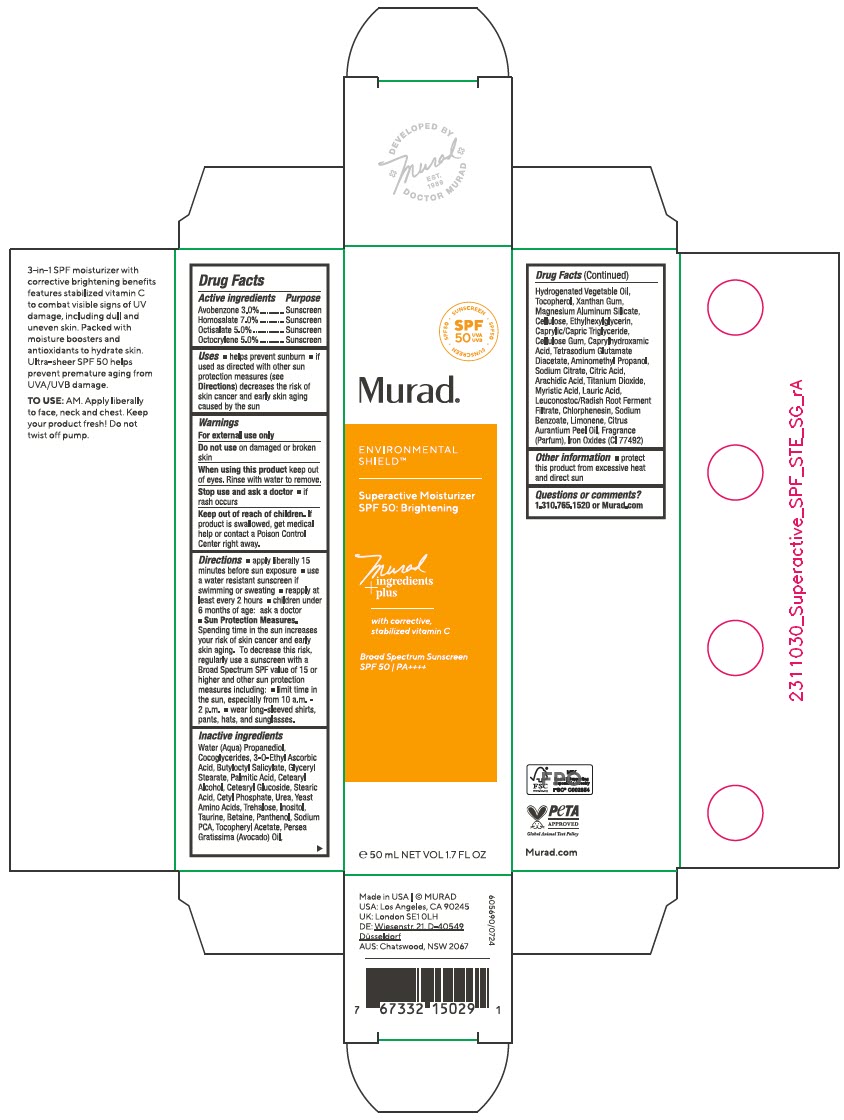 DRUG LABEL: Superactive Moisturizer SPF 50 Brightening
NDC: 70381-130 | Form: CREAM
Manufacturer: Murad, LLC
Category: otc | Type: HUMAN OTC DRUG LABEL
Date: 20250326

ACTIVE INGREDIENTS: AVOBENZONE 3 g/100 mL; HOMOSALATE 7 g/100 mL; OCTISALATE 5 g/100 mL; OCTOCRYLENE 5 g/100 mL
INACTIVE INGREDIENTS: WATER; PROPANEDIOL; COCO-GLYCERIDES; 3-O-ETHYL ASCORBIC ACID; BUTYLOCTYL SALICYLATE; GLYCERYL MONOSTEARATE; PALMITIC ACID; CETOSTEARYL ALCOHOL; STEARIC ACID; CETYL PHOSPHATE; UREA; AMINO ACIDS, SOURCE UNSPECIFIED; TREHALOSE; INOSITOL; TAURINE; BETAINE; PANTHENOL; SODIUM PYRROLIDONE CARBOXYLATE; .ALPHA.-TOCOPHEROL ACETATE; AVOCADO OIL; HYDROGENATED AVOCADO OIL; TOCOPHEROL; XANTHAN GUM; MAGNESIUM ALUMINUM SILICATE; POWDERED CELLULOSE; ETHYLHEXYLGLYCERIN; MEDIUM-CHAIN TRIGLYCERIDES; CARBOXYMETHYLCELLULOSE SODIUM, UNSPECIFIED; CAPRYLHYDROXAMIC ACID; TETRASODIUM GLUTAMATE DIACETATE; AMINOMETHYLPROPANOL; TRISODIUM CITRATE DIHYDRATE; CITRIC ACID MONOHYDRATE; ARACHIDIC ACID; TITANIUM DIOXIDE; MYRISTIC ACID; LAURIC ACID; LEUCONOSTOC/RADISH ROOT FERMENT FILTRATE; CHLORPHENESIN; SODIUM BENZOATE; LIMONENE, (+)-; BITTER ORANGE OIL; FERRIC OXIDE YELLOW; CETEARYL GLUCOSIDE

Superactive Moisturizer SPF 50: Brightening
SPF 50

Drug Facts

ACTIVE INGREDIENT

Active ingredients | Purpose
Avobenzone 3.0% | Sunscreen
Homosalate 7.0% | Sunscreen
Octisalate 5.0% | Sunscreen
Octocrylene 5.0% | Sunscreen

Uses

- helps prevent sunburn
- if used as directed with other sun protection measures (see Directions) decreases the risk of skin cancer and early skin aging caused by the sun

Warnings

For external use only

Do not use on damaged or broken skin

When using this product keep out of eyes. Rinse with water to remove.

Stop use and ask a doctor

- if rash occurs

Keep out of reach of children. If product is swallowed, get medical help or contact a Poison Control Center right away.

Directions

- apply liberally 15 minutes before sun exposure
- use a water resistant sunscreen if swimming or sweating
- reapply at least every 2 hours
- children under 6 months of age: ask a doctor
- Sun Protection Measures. Spending time in the sun increases your risk of skin cancer and early skin aging. To decrease this risk, regularly use a sunscreen with a Broad Spectrum SPF value of 15 or higher and other sun protection measures including:
  - limit time in the sun, especially from 10 a.m. - 2 p.m.
  - wear long-sleeved shirts, pants, hats, and sunglasses.

Inactive ingredients

Water (Aqua), Propanediol, Cocoglycerides, 3-O-Ethyl Ascorbic Acid, Butyloctyl Salicylate, Glyceryl Stearate, Palmitic Acid, Cetearyl Alcohol, Cetearyl Glucoside, Stearic Acid, Cetyl Phosphate, Urea, Yeast Amino Acids, Trehalose, Inositol, Taurine, Betaine, Panthenol, Sodium PCA, Tocopheryl Acetate, Persea Gratissima (Avocado) Oil, Hydrogenated Vegetable Oil, Tocopherol, Xanthan Gum, Magnesium Aluminum Silicate, Cellulose, Ethylhexylglycerin, Caprylic/Capric Triglyceride, Cellulose Gum, Caprylhydroxamic Acid, Tetrasodium Glutamate Diacetate, Aminomethyl Propanol, Sodium Citrate, Citric Acid, Arachidic Acid, Titanium Dioxide, Myristic Acid, Lauric Acid, Leuconostoc/Radish Root Ferment Filtrate, Chlorphenesin, Sodium Benzoate, Limonene, Citrus Aurantium Peel Oil, Fragrance (Parfum), Iron Oxides (CI 77492)

Other information

- protect this product from excessive heat and direct sun

Questions or comments?

1.310.765.1520 or Murad.com

PRINCIPAL DISPLAY PANEL - 50 mL Bottle Carton

SPF
50
UVA
UVB

• SUNSCREEN • SPF50 • SUNSCREEN • SPF50

Murad®

ENVIRONMENTAL
SHIELD™

Superactive Moisturizer
SPF 50: Brightening

Murad
ingredients
+plus

with corrective,
stabilized vitamin C

Broad Spectrum Sunscreen
SPF 50 / PA++++

℮ 50 mL NET VOL 1.7 FL OZ